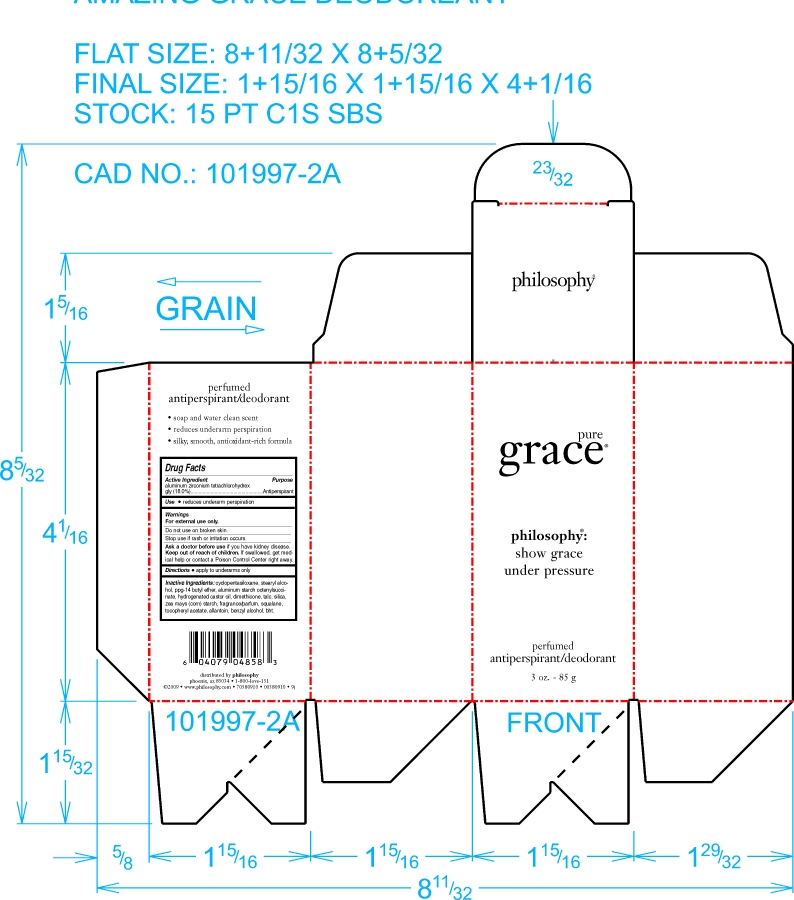 DRUG LABEL: Pure Grace Antiperspirant and Deodorant
NDC: 53135-925 | Form: STICK
Manufacturer: Raani Corporation
Category: otc | Type: HUMAN OTC DRUG LABEL
Date: 20100209

ACTIVE INGREDIENTS: Aluminum Zirconium Tetrachlorohydrex Gly 180 mg/1 g
INACTIVE INGREDIENTS: Cyclomethicone 5; Stearyl Alcohol; Hydrogenated Castor Oil; Dimethicone; Talc; Silicon Dioxide; Starch, Corn; Squalane; .alpha.-tocopherol acetate, d-; Allantoin; Benzyl Alcohol; Butylated Hydroxytoluene; PPG-14 Butyl Ether

Drug Facts

Active Ingredient.............

Aluminum Zirconium Tetrachlorhydrex-gly.......18.0%

INACTIVE INGREDIENT

CYCLOPTENTASILOXANE 36.15%

STEARYL ALCOHOL 20.0%

PPG-14 BUTYL ETHER 10.0%

ALUMINUM STARCH OCTENYL SUCCINATE 3.0%

HYDROGENATED CASTOR OIL 3.0%

DIMETHICONE 2.10%

TALC 2.0%

SILICA 1.0%

CORN STARCH 1.0%

FRAGRANCE 1.0%

SQUALANE 0.05%

TOCOPHERYL ACETATE 0.04%

ALLANTOIN 0.0005%

BENZYL ALCOHOL 0.0003%

BHT 0.0002%

PURPOSE

USE: REDUCES UNDERARM PERSPIRATION.

ASK DOCTOR BEFORE USE IF YOU HAVE KIDNEY DISEASE

KEEP OUT OF REACH OF CHILDREN. IF SWALLOWED GET MEDICAL HELP OR CONTACT A POISON CONTROL CENTER RIGHT AWAY.

DO NOT USE ON BROKEN SKIN.

STOP USE

Enter section text here